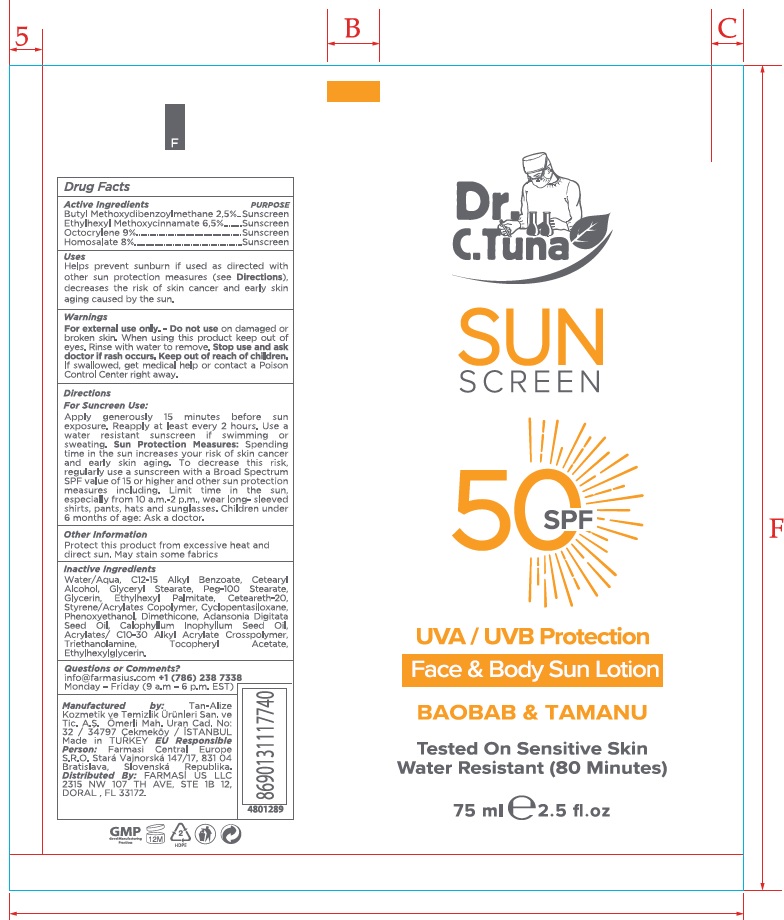 DRUG LABEL: Dr. C. Tuna Sunscreen 50 SPF UVA UVB Protection Face and Body Sun
NDC: 74690-006 | Form: LOTION
Manufacturer: Farmasi US LLC
Category: otc | Type: HUMAN OTC DRUG LABEL
Date: 20260109

ACTIVE INGREDIENTS: AVOBENZONE 25 mg/1 mL; OCTINOXATE 65 mg/1 mL; OCTOCRYLENE 90 mg/1 mL; HOMOSALATE 80 mg/1 mL
INACTIVE INGREDIENTS: WATER; ALKYL (C12-15) BENZOATE; CETOSTEARYL ALCOHOL; GLYCERYL MONOSTEARATE; PEG-100 STEARATE; GLYCERIN; ETHYLHEXYL PALMITATE; POLYOXYL 20 CETOSTEARYL ETHER; CYCLOMETHICONE 5; PHENOXYETHANOL; DIMETHICONE; ADANSONIA DIGITATA SEED OIL; TAMANU OIL; TROLAMINE; .ALPHA.-TOCOPHEROL ACETATE; ETHYLHEXYLGLYCERIN

Dr. C. Tuna Sunscreen 50 SPF UVA/UVB Protection Face & Body Sun Lotion

Active Ingredients

Butyl Methoxydibenzoylmethane 2,5%

Ethylhexyl Methoxycinnamate 6,5%

Octocrylene 9%

Homosalate 8%

PURPOSE

Sunscreen

Uses

Helps prevent sunburn if used as directed with other sun protection measures (see), decreases the risk of skin cancer and early skin aging caused by the sun. Directions

Warnings

on damaged or broken skin. When using this product keep out of eyes. Rinse with water to remove. For external use only. - Do not use Stop use and ask doctor if rash occurs.

Keep out of reach of children.

If swallowed, get medical help or contact a Poison Control Center right away.

Directions

For Sunscreen Use:

Apply generously 15 minutes before sun exposure. Reapply at least every 2 hours. Use a water resistant sunscreen if swimming or sweating.

Spending time in the sun increases your risk of skin cancer and early skin aging. To decrease this risk, regularly use a sunscreen with a Broad Spectrum SPF value of 15 or higher and other sun protection measures including. Limit time in the sun, especially from 10 a.m.–2 p.m., wear long - sleeved shirts, pants, hats and sunglasses. Children under 6 months: Ask a doctor. Sun Protection Measures:

Other information

Protect this product from excessive heat and direct sun. May stain some fabrics

Inactive Ingredients

Water/Aqua, C12-15 Alkyl Benzoate, Cetearyl Alcohol, Glyceryl Stearate, Peg-100 Stearate, Glycerin, Ethylhexyl Palmitate, Ceteareth-20, Styrene/Acrylates Copolymer, Cyclopentasiloxane, Phenoxyethanol, Dimethicone, Adansonia Digitata Seed Oil, Calophyllum Inophyllum Seed Oil, Acrylates/ C10-30 Alkyl Acrylate Crosspolymer, Triethanolamine, Tocopheryl Acetate, Ethylhexylglycerin.

Questions or Comments?

info@farmasius.com + 1 (786) 238 7338

Monday - Friday (9 a.m - 6 p.m. EST)

Manufactured by: Tan-Alize Kozmetik ve Temizlik Ürünleri San. ve. Tic. A.S. Ömerli Mah. Uran Cad. No: 32 / 34797 Cekmeköy / ISTANBUL

Made in TURKEY

EU REsponsible Person: Farmasi Central Europe S.R.O. Stará Vajnorská Republika. Distributed By: FARMASI US LLC 2315 NW 107 TH AVE, STE 1B 12, DORAL , FL 33172.